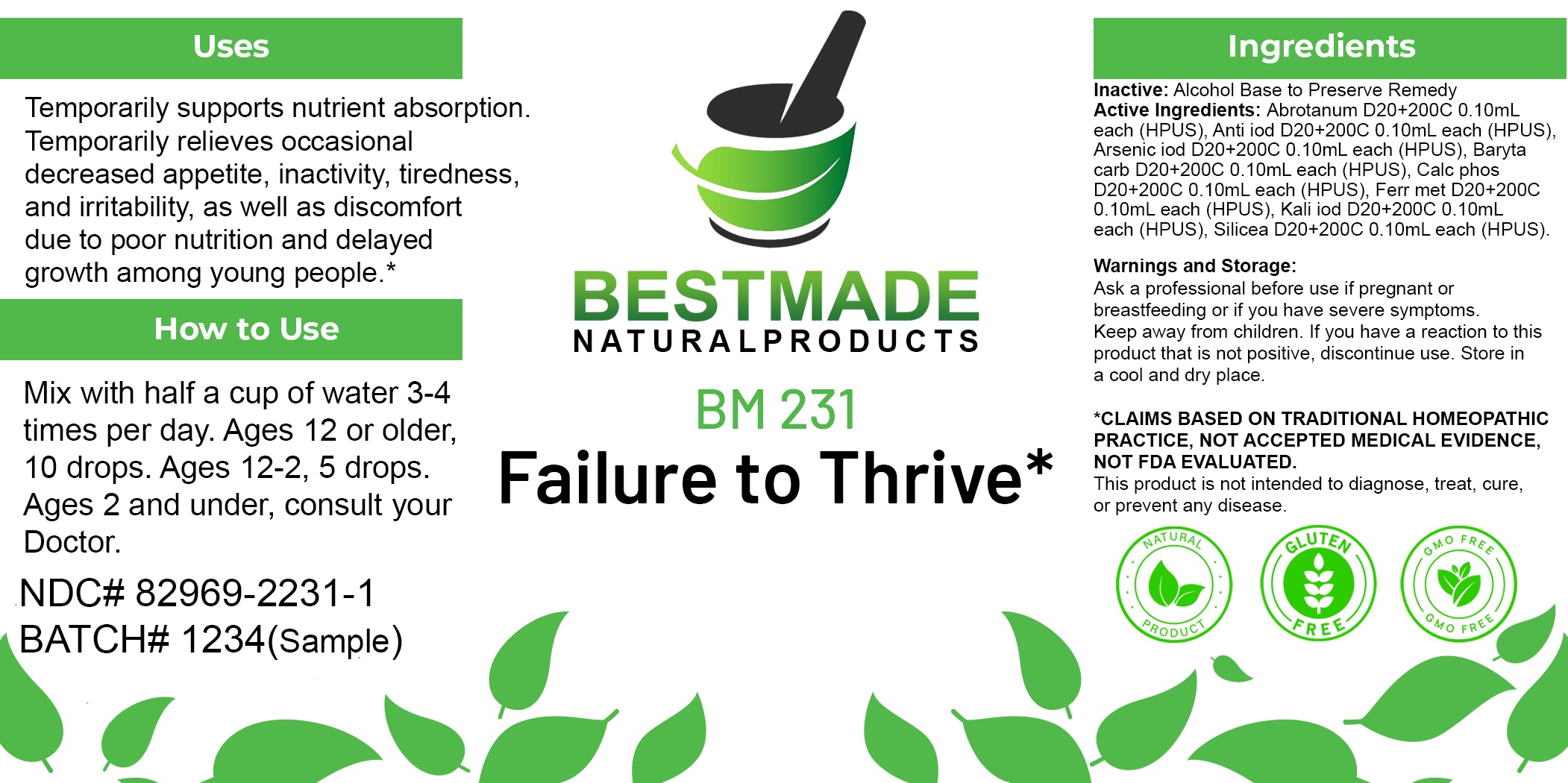 DRUG LABEL: Bestmade Natural Products BM231
NDC: 82969-2231 | Form: LIQUID
Manufacturer: Bestmade Natural Products
Category: homeopathic | Type: HUMAN OTC DRUG LABEL
Date: 20250304

ACTIVE INGREDIENTS: ANTIMONY TRIIODIDE 30 [hp_C]/30 [hp_C]; POTASSIUM IODIDE 30 [hp_C]/30 [hp_C]; ARSENIC TRIIODIDE 30 [hp_C]/30 [hp_C]; SILICA 30 [hp_C]/30 [hp_C]; ARTEMISIA ABROTANUM FLOWERING TOP 30 [hp_C]/30 [hp_C]; IRON 30 [hp_C]/30 [hp_C]; TRIBASIC CALCIUM PHOSPHATE 30 [hp_C]/30 [hp_C]; BARIUM CARBONATE 30 [hp_C]/30 [hp_C]
INACTIVE INGREDIENTS: ALCOHOL 30 [hp_C]/30 [hp_C]

BM231

DOSAGE AND ADMINISTRATION

How to Use

Mix with half a cup of water 3-4 times per day. Ages 12 or older, 10 drops. Ages 12-2, 5 drops. Ages 2 and under, consult your Doctor.

Inactive:

Alcohol Base to Preserve Product

Active Ingredients:
Abrotanum D20+200C 0.10mL each (HPUS), Anti iod D20+200C 0.10mL each (HPUS), Arsenic iod D20+200C 0.10mL each (HPUS), Baryta carb D20+200C 0.10mL each (HPUS), Calc phos D20+200C 0.10mL each (HPUS), Ferr met D20+200C 0.10mL each (HPUS), Kali iod D20+200C 0.10mL each (HPUS), Silicea D20+200C 0.10mL each (HPUS).

KEEP OUT OF REACH OF CHILDREN

Warnings and Storage:

Ask a professional before use if pregnant or breastfeeding or if you have severe symptoms.

Keep away from children. If you have a reaction to this product that is not positive, discontinue use. Store in a cool and dry place

*CLAIMS BASED ON TRADITIONAL HOMEOPATHIC PRACTICE, NOT ACCEPTED MEDICAL EVIDENCE NOT FDA EVALUATED.
This product is not intended to diagnose, treat, cure, or prevent any disease.

Warnings and Storage:

Ask a professional before use if pregnant or breastfeeding or if you have severe symptoms.

Keep away from children. If you have a reaction to this product that is not positive, discontinue use. Store in a cool and dry place

*CLAIMS BASED ON TRADITIONAL HOMEOPATHIC PRACTICE, NOT ACCEPTED MEDICAL EVIDENCE NOT FDA EVALUATED.
This product is not intended to diagnose, treat, cure, or prevent any disease.

Uses
Temporarily supports nutrient absorption. Temporarily relieves occasional decreased appetite, inactivity, tiredness, and irritability, as well as discomfort due to poor nutrition and delayed growth among young people.*

Uses
Temporarily supports nutrient absorption. Temporarily relieves occasional decreased appetite, inactivity, tiredness, and irritability, as well as discomfort due to poor nutrition and delayed growth among young people.*

Entire package label